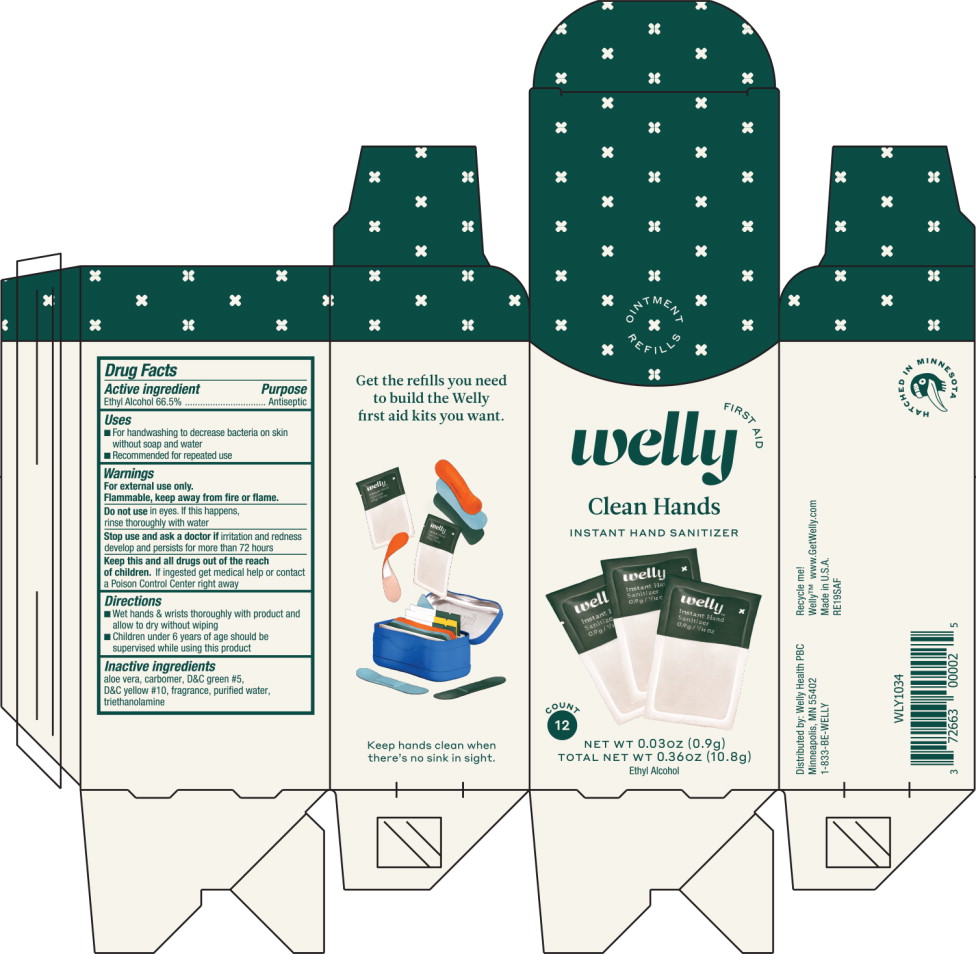 DRUG LABEL: Antiseptic
NDC: 72663-111 | Form: GEL
Manufacturer: Welly Health PCB
Category: otc | Type: HUMAN OTC DRUG LABEL
Date: 20191105

ACTIVE INGREDIENTS: alcohol 665 mL/1000 mL
INACTIVE INGREDIENTS: aloe vera leaf; carbomer interpolymer type a (allyl sucrose crosslinked); D&C green no. 5; D&C yellow no. 10; water; trolamine

Drug Facts

Active Ingredient

Ethyl Alcohol 66.5%

Purpose

Antiseptic

Uses

- For handwashing to decrease bacteria on skin without soap and water
- Recommended for repeated use

Warnings

For external use only.

Flammable, keep away from fire or flame.

Do not use in eyes. If this happens, rinse thoroughly with water

Stop use and ask a doctor if irritation and redness develop and persists for more than 72 hours

KEEP OUT OF REACH OF CHILDREN

Keep this and all drugs out of the reach of children. If ingested get medical help or contact a Poison Control Center right away

Directions

- Wet hands & wrists thoroughly with product and allow to dry without wiping
- Children under 6 years of age should be supervised while using this product

Inactive Ingredients

aloe vera, carbomer, D&C green #5, D&C yellow #10, fragrance, purified water, triethanolamine

Principal Display Panel – Box Label

OINTMENT REFILLS

Welly FIRST AID

Clean Hands
INSTANT HAND SANITIZER

COUNT 12

NET WT 0.03 oz (0.9g)

TOTAL NET WT 0.36 oz (10.8g)

Ethyl Alcohol